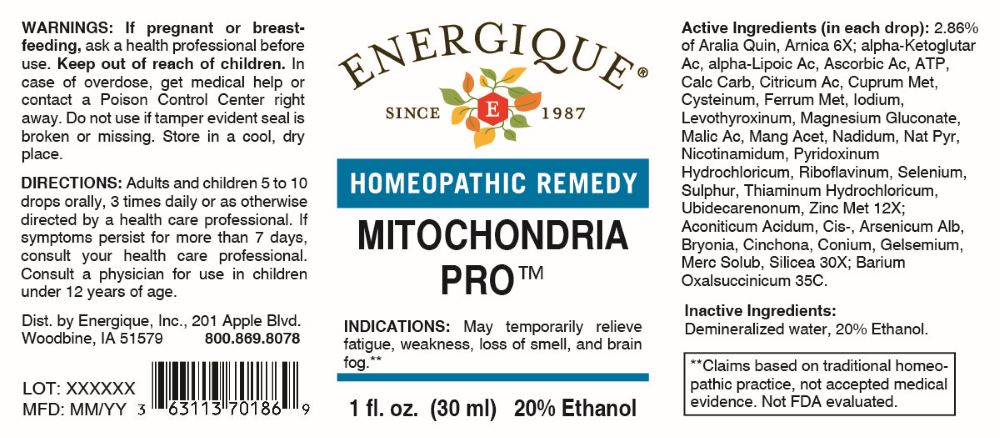 DRUG LABEL: Mitochondria Pro
NDC: 44911-0903 | Form: LIQUID
Manufacturer: Energique, Inc.
Category: homeopathic | Type: HUMAN OTC DRUG LABEL
Date: 20260218

ACTIVE INGREDIENTS: AMERICAN GINSENG 6 [hp_X]/1 mL; ARNICA MONTANA WHOLE 6 [hp_X]/1 mL; ADENOSINE TRIPHOSPHATE DISODIUM 12 [hp_X]/1 mL; OXOGLURIC ACID 12 [hp_X]/1 mL; ASCORBIC ACID 12 [hp_X]/1 mL; ALPHA LIPOIC ACID 12 [hp_X]/1 mL; OYSTER SHELL CALCIUM CARBONATE, CRUDE 12 [hp_X]/1 mL; ANHYDROUS CITRIC ACID 12 [hp_X]/1 mL; COPPER 12 [hp_X]/1 mL; CYSTEINE 12 [hp_X]/1 mL; IRON 12 [hp_X]/1 mL; IODINE 12 [hp_X]/1 mL; LEVOTHYROXINE 12 [hp_X]/1 mL; MAGNESIUM GLUCONATE 12 [hp_X]/1 mL; MALIC ACID 12 [hp_X]/1 mL; MANGANESE ACETATE TETRAHYDRATE 12 [hp_X]/1 mL; NADIDE 12 [hp_X]/1 mL; SODIUM PYRUVATE 12 [hp_X]/1 mL; NIACINAMIDE 12 [hp_X]/1 mL; PYRIDOXINE HYDROCHLORIDE 12 [hp_X]/1 mL; RIBOFLAVIN 12 [hp_X]/1 mL; SELENIUM 12 [hp_X]/1 mL; SULFUR 12 [hp_X]/1 mL; THIAMINE HYDROCHLORIDE 12 [hp_X]/1 mL; UBIDECARENONE 12 [hp_X]/1 mL; ZINC 12 [hp_X]/1 mL; ACONITIC ACID, (Z)- 30 [hp_X]/1 mL; ARSENIC TRIOXIDE 30 [hp_X]/1 mL; BRYONIA ALBA ROOT 30 [hp_X]/1 mL; CINCHONA OFFICINALIS BARK 30 [hp_X]/1 mL; CONIUM MACULATUM FLOWERING TOP 30 [hp_X]/1 mL; GELSEMIUM SEMPERVIRENS ROOT 30 [hp_X]/1 mL; MERCURIUS SOLUBILIS 30 [hp_X]/1 mL; SILICON DIOXIDE 30 [hp_X]/1 mL; BARIUM OXALOSUCCINATE 35 [hp_C]/1 mL
INACTIVE INGREDIENTS: WATER; ALCOHOL

DRUG FACTS:

ACTIVE INGREDIENTS:

(in each drop) 2.86% of Aralia Quinquefolia 6X, Arnica Montana 6X; Alpha-Ketoglutaricum Acidum 12X, Alpha-Lipoicum Acidum 12X, Ascorbicum Acidum 12X, Adenosinum Triphosphoricum Dinatrum 12X, Calcarea Carbonica 12X, Citricum Acidum 12X, Cuprum Metallicum 12X, Cysteinum 12X, Ferrum Metallicum 12X, Iodium 12X, Levothyroxinum 12X, Magnesium Gluconicum Dihydricum 12X, Malicum Acidum 12X, Manganum Aceticum 12X, Nadidum 12X, Natrum Pyruvicum 12X, Nicotinamidum 12X, Pyridoxinum Hydrochloricum 12X, Riboflavinum 12X, Selenium Metallicum 12X, Sulphur 12X, Thiaminum Hydrochloricum 12X, Ubidecarenonum 12X, Zincum Metallicum 12X; Aconiticum Acidum, Cis- 30X; Arsenicum Album 30X, Bryonia 30X, Cinchona Officinalis 30X, Conium Maculatum 30X, Gelsemium Sempervirens 30X, Mercurius Solubilis 30X, Silicea 30X; Barium Oxalsuccinicum 35C.

PURPOSE:

May temporarily relieve fatigue, weakness, loss of smell, and brain fog.**

**Claims based on traditional homeopathic practice, not accepted medical evidence. Not FDA evaluated.

WARNINGS:

If pregnant or breast-feeding, ask a health professional before use.

Keep out of reach of children. In case of overdose, get medical help or contact a Poison Control Center right away.

Do not use if tamper evident seal is broken or missing. Store in a cool, dry place.

KEEP OUT OF REACH OF CHILDREN:

In case of overdose, get medical help or contact a Poison Control Center right away.

DIRECTIONS:

Adults and children 5 to 10 drops orally, 3 times daily or as otherwise directed by a health care professional. If symptoms persist for more than 7 days, consult your health care professional. Consult a physician for use in children under 12 years of age.

INDICATIONS:

May temporarily relieve fatigue, weakness, loss of smell, and brain fog.**

**Claims based on traditional homeopathic practice, not accepted medical evidence. Not FDA evaluated.

INACTIVE INGREDIENTS:

Demineralized water, 20% Ethanol.

QUESTIONS:

Dist. by Energique, Inc.
201 Apple Blvd.

Woodbine, IA 51579

800.869.8078

PACKAGE LABEL DISPLAY:

ENERGIQUE
SINCE 1987
HOMEOPATHIC REMEDY

MITOCHONDRIA PRO

1 fl. oz. (30 ml)